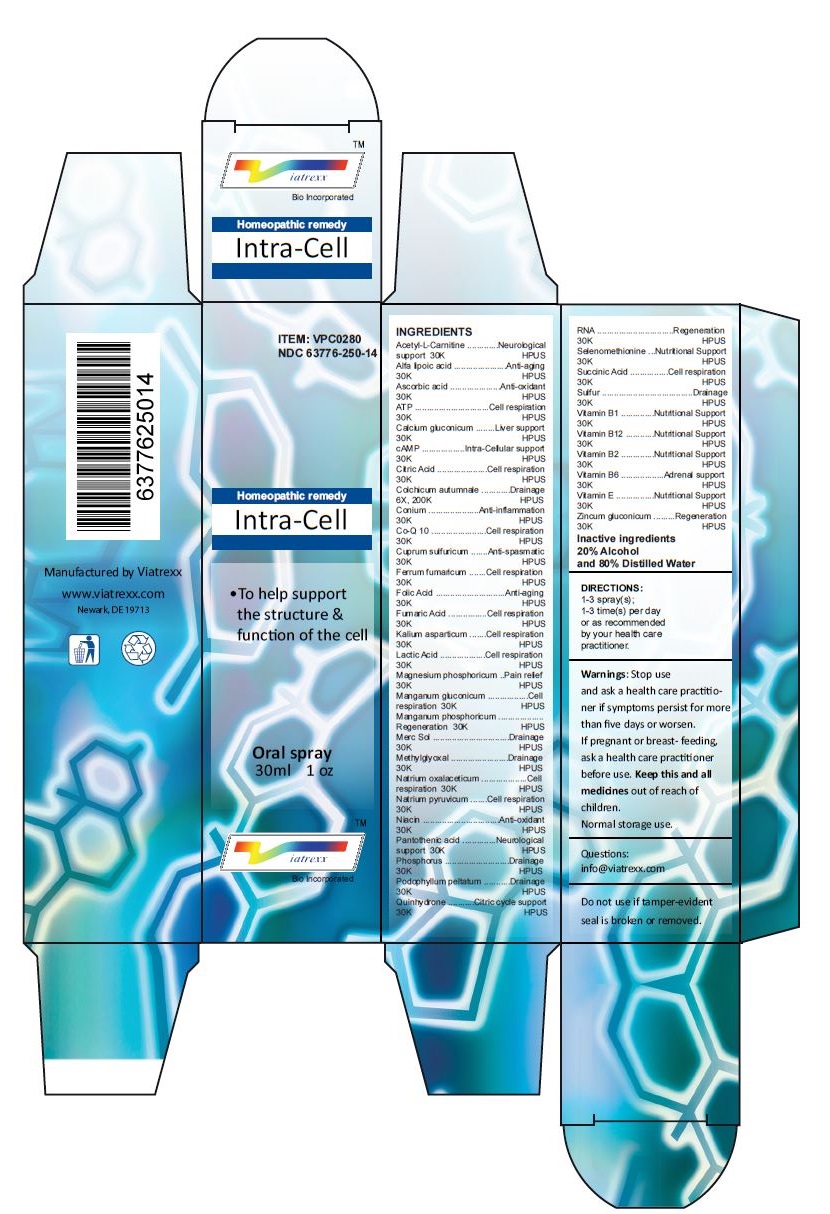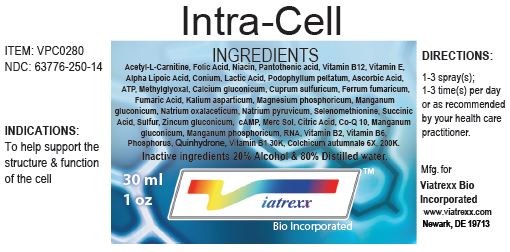 DRUG LABEL: Intra-cell
NDC: 63776-250 | Form: SPRAY
Manufacturer: VIATREXX BIO INCORPORATED
Category: homeopathic | Type: HUMAN OTC DRUG LABEL
Date: 20221130

ACTIVE INGREDIENTS: ACETYLCARNITINE 30 [kp_C]/1 mL; .ALPHA.-LIPOIC ACID 30 [kp_C]/1 mL; ASCORBIC ACID 30 [kp_C]/1 mL; ADENOSINE TRIPHOSPHATE 30 [kp_C]/1 mL; CALCIUM GLUCONATE 30 [kp_C]/1 mL; CITRIC ACID MONOHYDRATE 30 [kp_C]/1 mL; COLCHICUM AUTUMNALE BULB 200 [kp_C]/1 mL; CONIUM MACULATUM FLOWERING TOP 30 [kp_C]/1 mL; UBIDECARENONE 30 [kp_C]/1 mL; CUPRIC SULFATE 30 [kp_C]/1 mL; FERRIC CHLORIDE HEXAHYDRATE 30 [kp_C]/1 mL; FOLIC ACID 30 [kp_C]/1 mL; FUMARIC ACID 30 [kp_C]/1 mL; POTASSIUM ASPARTATE 30 [kp_C]/1 mL; LACTIC ACID 30 [kp_C]/1 mL; MAGNESIUM PHOSPHATE, TRIBASIC, PENTAHYDRATE 30 [kp_C]/1 mL; MANGANESE GLUCONATE 30 [kp_C]/1 mL; MANGANESE PHOSPHATE, DIBASIC 30 [kp_C]/1 mL; MERCURIUS SOLUBILIS 30 [kp_C]/1 mL; PYRUVALDEHYDE 30 [kp_C]/1 mL; SODIUM DIETHYL OXALACETATE 30 [kp_C]/1 mL; SODIUM PYRUVATE 30 [kp_C]/1 mL; NIACIN 30 [kp_C]/1 mL; PANTOTHENIC ACID 30 [kp_C]/1 mL; PHOSPHORUS 30 [kp_C]/1 mL; PODOPHYLLUM 30 [kp_C]/1 mL; QUINHYDRONE 30 [kp_C]/1 mL; SACCHAROMYCES CEREVISIAE RNA 30 [kp_C]/1 mL; SELENOMETHIONINE 30 [kp_C]/1 mL; SUCCINIC ACID 30 [kp_C]/1 mL; SULFUR 30 [kp_C]/1 mL; THIAMINE 30 [kp_C]/1 mL; CYANOCOBALAMIN 30 [kp_C]/1 mL; RIBOFLAVIN 30 [kp_C]/1 mL; PYRIDOXINE 30 [kp_C]/1 mL; .ALPHA.-TOCOPHEROL 30 [kp_C]/1 mL; ZINC GLUCONATE 30 [kp_C]/1 mL
INACTIVE INGREDIENTS: WATER; ALCOHOL

Intra-cell

Active Ingredients

Acetyl-L-Carnitine (30K), Alfa lipoic acid (30K), Ascorbic acid (30K), ATP (30K), Calcium gluconicum (30K), cAMP (30K), Citric Acid (30K), Colchicum autumnale (6X, 200K), Conium (30K), Co-Q 10 (30K), Cuprum sulfuricum (30K), Ferrum fumaricum (30K), Folic Acid (30K), Fumaric Acid (30K), Kalium asparticum (30K), Lactic Acid (30K), Magnesium phosphoricum (30K), Manganum gluconicum (30K), Manganum phosphoricum (30K), Merc Sol (30K), Methylglyoxal (30K), Natrium oxalaceticum (30K), Natrium pyruvicum (30K), Niacin (30K), Pantothenic acid (30K), Phosphorus (30K), Podophyllum peltatum (30K), Quinhydrone (30K), RNA (30K), Selenomethionine (30K), Succinic Acid (30K), Sulfur (30K), Vitamin B1 (30K), Vitamin B12 (30K), Vitamin B2 (30K), Vitamin B6 (30K), Vitamin E (30K), Zincum gluconicum (30K)

Purpose:

Acetyl-L-Carnitine | Neurological
Alfa Ipoic acid | Anti-aging
Ascorbic acid | Anti-oxidant
ATP | Cell respiration
Calcium gluconicum | Liver support
cAMP | Intra-Cellular support
Citric Acid | Cell respiration
Colchicum autumnale | Drainage
Conium | Anti-inflammation
Co-Q 10 | Cell respiration
Cuprum sulfuricum | Anti-spasmatic
Ferrum fumaricum | Cell respiration
Folic Acid | Anti-aging
Fumaric Acid | Cell respiration
Kalium asparticum | Cell respiration
Lactic Acid | Cell respiration
Magnesium phosphoricum | Pain relief
Manganum gluconicum | Cell Respiration
Manganum phosphoricum | Regeneration
Merc Sol | Drainage
Methylglyoxal | Drainage
Natrium oxalaceticum | Cell respiration
Natrium pyruvicum | Cell respiration
Niacin | Anti-oxidant
Pantothenic acid | Neurological support
Phosphorus | Drainage
Podophyllum peltatum | Drainage
Quinhydrone | Citric cycle support
RNA | Regeneration
Selenomethionine | Nutritional Support
Succinic Acid | Cell respiration
Sulfur | Drainage
Vitamin B1 | Nutritional Support
Vitamin B12 | Nutritional Support
Vitamin B2 | Nutritional Support
Vitamin B6 | Adrenal support
Vitamin E | Nutritional Support
Zincum gluconicum | Regeneration

Uses

To help support the structure & function of the cell

Warnings

Stop use and ask a health care practitioner if symptoms persist for more than five days or worsen. If pregnant or breastfeeding, ask a health care practitioner before use.

Dosage

1-3 spray(s); 1-3 time(s) per day or as recommended by your health care practitioner.

KEEP OUT OF REACH OF CHILDREN

Keep this and all medicines out of reach of children.

Inactive ingredients

20% Alcohol and 80% Water

Other Information

Normal storage use.
Do not use if tamper-evident seal is broken or removed.

Questions

info@viatrexx.com

Principal Display Panel

ITEM: VPC0280
NDC 63776-250-14
Homeopathic remedy
Intra-Cell
• To help support the structure & function of the cell
Oral spray
30ml 1 oz
Viatrexx™ Bio Incorporated
Manufactured by Viatrexx
www.viatrexx.com
Newark, DE 19713

Intra-Cell
30 ml
1 oz
Viatrexx™ Bio Incorporated
ITEM: VPC0280
NDC: 63776-250-14
INDICATIONS:
To help support the structure & function of the cell
DIRECTIONS:
1-3 spray(s); 1-3 time(s) per day or as recommended by your health care practitioner.
Mfg. for
Viatrexx Bio Incorporated
www.viatrexx.com
Newark, DE 19713